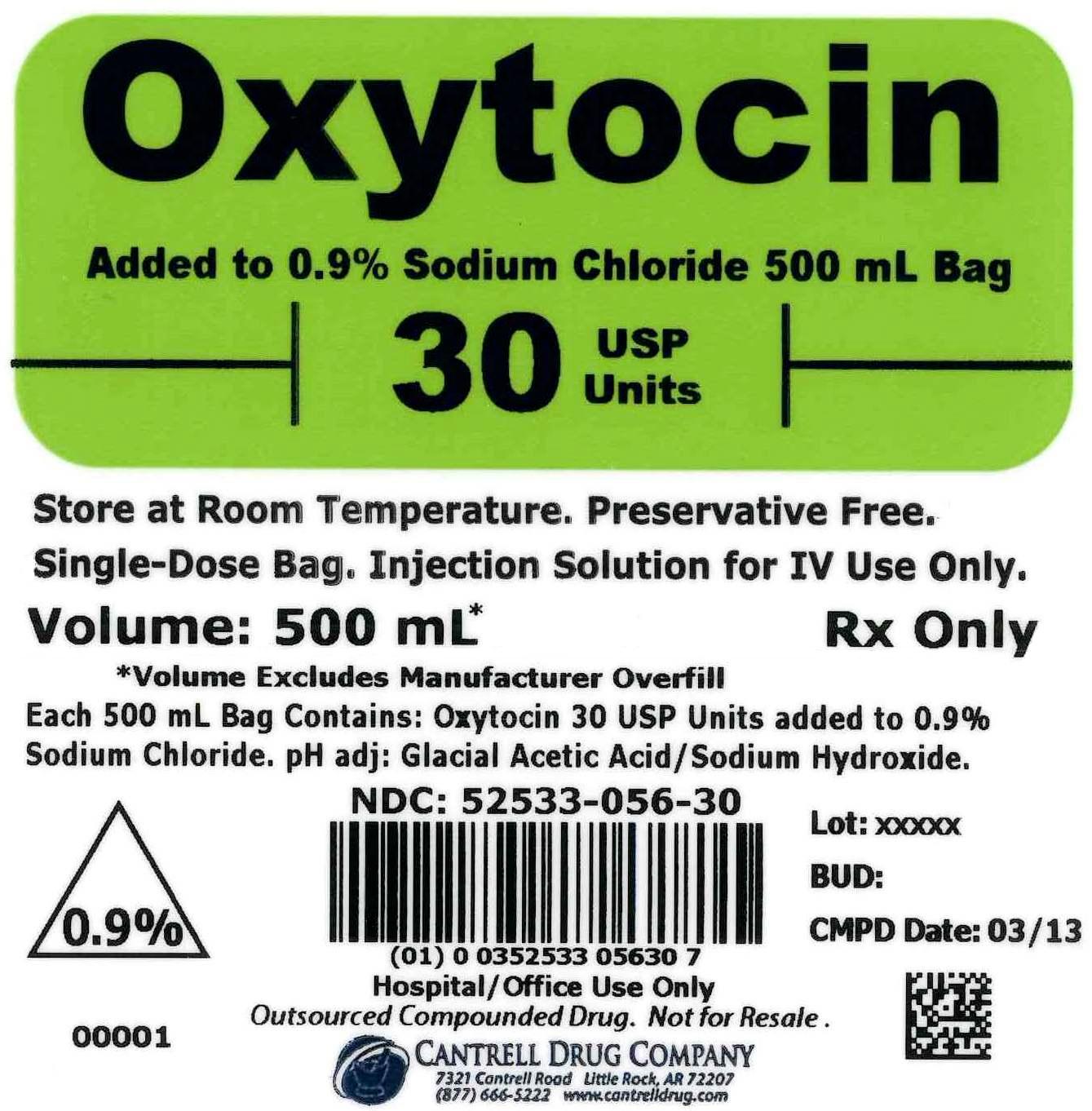 DRUG LABEL: Oxytocin
NDC: 52533-056 | Form: INJECTION, SOLUTION
Manufacturer: Cantrell Drug Company
Category: prescription | Type: HUMAN PRESCRIPTION DRUG LABEL
Date: 20141211

ACTIVE INGREDIENTS: OXYTOCIN 30 [USP'U]/500 mL
INACTIVE INGREDIENTS: Sodium Chloride 4.5 g/500 mL; Water

Oxytocin 30 USP Units Added to 0.9% Sodium Chloride 500 mL Bag